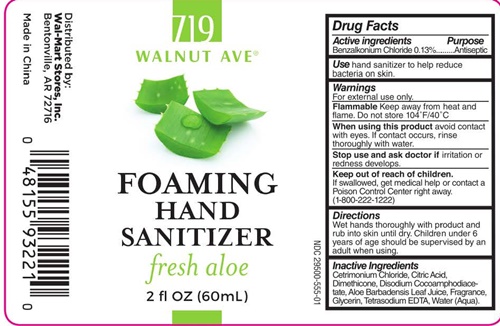 DRUG LABEL: 719 WALNUT AVE HAND
NDC: 29500-0555 | Form: LIQUID
Manufacturer: Personal Care Products
Category: otc | Type: HUMAN OTC DRUG LABEL
Date: 20170521

ACTIVE INGREDIENTS: BENZALKONIUM CHLORIDE 78 mg/60 mL
INACTIVE INGREDIENTS: CETRIMONIUM CHLORIDE; CITRIC ACID MONOHYDRATE; DIMETHICONE; DISODIUM COCOAMPHODIACETATE; ALOE VERA LEAF; GLYCERIN; EDETATE DISODIUM; WATER

PC-WM Foaming Hand Sanitizer 0555

Drug Facts active ingredients

Benzalkonium Chloride

Purpose

Antiseptic

Use

hand sanitizer to help reduce bacteria on skin

Warnings

For external use only.

Flammable Keep away from heat and flame. Do not store 104°F/40°C

Stop use and ask a doctor if

irritation ot redness develops.

Keep out of reach of children.

If swallowed, get medical help or contact a Poison Control Center right away. (1-800-222-1222).

Directions

Wet hands thoroughly with the product and rub skin until dry. Children under 6 years of age should be supervised by an adult when using.

Inactive Ingredients

Cetrimonium Chloride, Citric Acid, Dimethicone, Disodium Cocoamphodiacetate, Aloe Barbadensis Leaf Juice, Fragrance, Glycerin, Tetrasodium EDTA Water (Aqua).

719 WALNUT AVE® FOAMING HAND SANITIZER fresh aloe product label

719 WALNUT AVE®

FOAMING HAND SANITIZER
fresh aloe

2 fl OZ (60 mL)

NDC 29500-0555-1

Distributed by:
Wal-Mart Stores, Inc.
Bentonville, AR 72716

Made in China